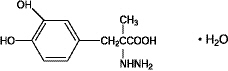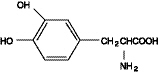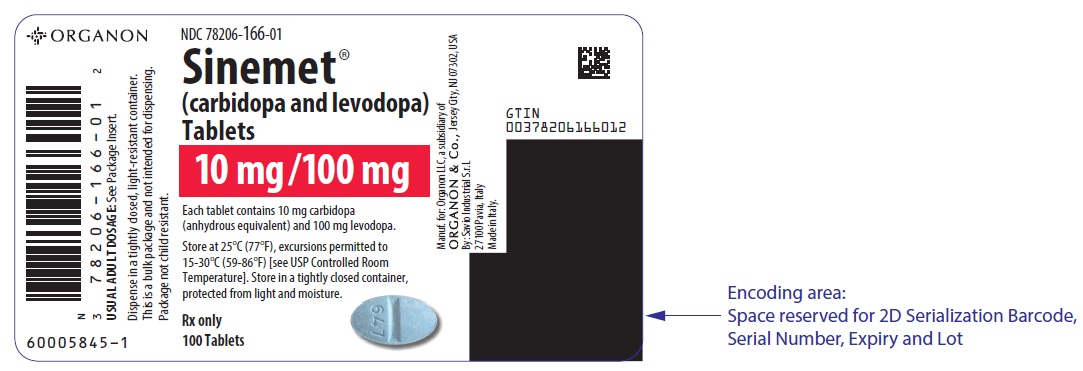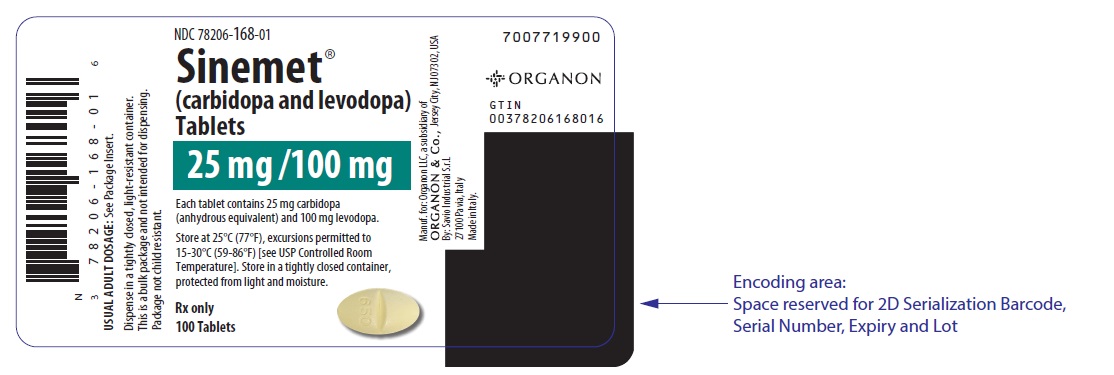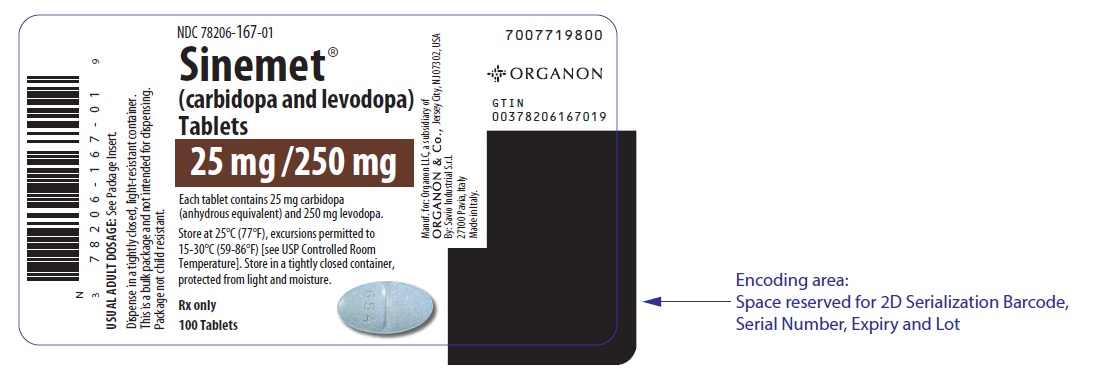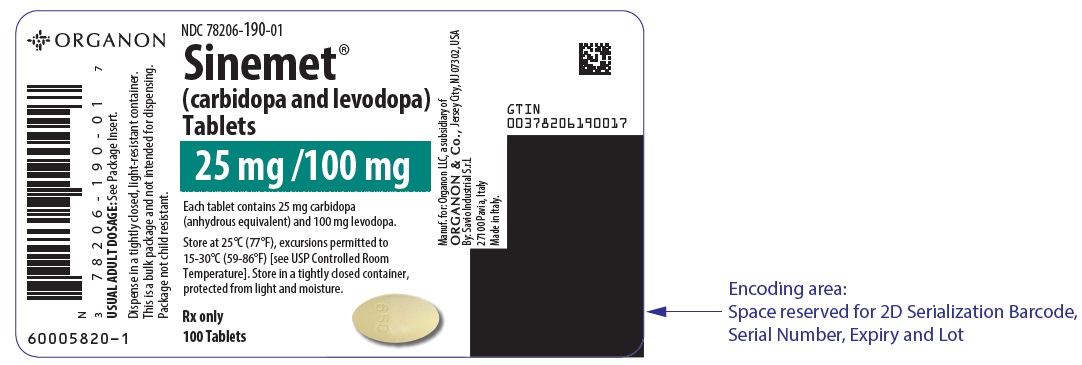 DRUG LABEL: SINEMET
NDC: 78206-166 | Form: TABLET
Manufacturer: Organon LLC
Category: prescription | Type: HUMAN PRESCRIPTION DRUG LABEL
Date: 20241024

ACTIVE INGREDIENTS: CARBIDOPA 10 mg/1 1; LEVODOPA 100 mg/1 1
INACTIVE INGREDIENTS: MICROCRYSTALLINE CELLULOSE; MAGNESIUM STEARATE; STARCH, CORN; FD&C BLUE NO. 2

SINEMET®
(carbidopa and levodopa)
Tablets

DESCRIPTION

SINEMET® (carbidopa and levodopa) is a combination of carbidopa and levodopa for the treatment of Parkinson's disease and syndrome.

Carbidopa, an inhibitor of aromatic amino acid decarboxylation, is a white, crystalline compound, slightly soluble in water, with a molecular weight of 244.3. It is designated chemically as (—)-L-α-hydrazino-α-methyl-β-(3,4-dihydroxybenzene) propanoic acid monohydrate. Its empirical formula is C10H14N2O4•H2O, and its structural formula is:

Tablet content is expressed in terms of anhydrous carbidopa which has a molecular weight of 226.3.

Levodopa, an aromatic amino acid, is a white, crystalline compound, slightly soluble in water, with a molecular weight of 197.2. It is designated chemically as (—)-L-α-amino-β-(3,4-dihydroxybenzene) propanoic acid. Its empirical formula is C9H11NO4, and its structural formula is:

SINEMET is supplied as tablets in three strengths:

SINEMET 25-100, containing 25 mg of carbidopa and 100 mg of levodopa.

SINEMET 10-100, containing 10 mg of carbidopa and 100 mg of levodopa.

SINEMET 25-250, containing 25 mg of carbidopa and 250 mg of levodopa.

Inactive ingredients are microcrystalline cellulose, pregelatinized starch, starch (corn), and magnesium stearate. SINEMET 10-100 and 25-250 Tablets also contain FD&C Blue #2. SINEMET 25-100 Tablets also contain D&C Yellow #10.

CLINICAL PHARMACOLOGY

Mechanism of Action

Parkinson's disease is a progressive, neurodegenerative disorder of the extrapyramidal nervous system affecting the mobility and control of the skeletal muscular system. Its characteristic features include resting tremor, rigidity, and bradykinetic movements. Symptomatic treatments, such as levodopa therapies, may permit the patient better mobility.

Current evidence indicates that symptoms of Parkinson's disease are related to depletion of dopamine in the corpus striatum. Administration of dopamine is ineffective in the treatment of Parkinson's disease apparently because it does not cross the blood-brain barrier. However, levodopa, the metabolic precursor of dopamine, does cross the blood-brain barrier, and presumably is converted to dopamine in the brain. This is thought to be the mechanism whereby levodopa relieves symptoms of Parkinson's disease.

Pharmacodynamics

When levodopa is administered orally, it is rapidly decarboxylated to dopamine in extracerebral tissues so that only a small portion of a given dose is transported unchanged to the central nervous system. For this reason, large doses of levodopa are required for adequate therapeutic effect, and these may often be accompanied by nausea and other adverse reactions, some of which are attributable to dopamine formed in extracerebral tissues.

Since levodopa competes with certain amino acids for transport across the gut wall, the absorption of levodopa may be impaired in some patients on a high protein diet.

Carbidopa inhibits decarboxylation of peripheral levodopa. It does not cross the blood-brain barrier and does not affect the metabolism of levodopa within the central nervous system.

The incidence of levodopa-induced nausea and vomiting is less with SINEMET than with levodopa. In many patients, this reduction in nausea and vomiting will permit more rapid dosage titration.

Since its decarboxylase inhibiting activity is limited to extracerebral tissues, administration of carbidopa with levodopa makes more levodopa available for transport to the brain.

Pharmacokinetics

Carbidopa reduces the amount of levodopa required to produce a given response by about 75% and, when administered with levodopa, increases both plasma levels and the plasma half-life of levodopa, and decreases plasma and urinary dopamine and homovanillic acid.

The plasma half-life of levodopa is about 50 minutes, without carbidopa. When carbidopa and levodopa are administered together, the half-life of levodopa is increased to about 1.5 hours. At steady state, the bioavailability of carbidopa from SINEMET tablets is approximately 99% relative to the concomitant administration of carbidopa and levodopa.

In clinical pharmacologic studies, simultaneous administration of carbidopa and levodopa produced greater urinary excretion of levodopa in proportion to the excretion of dopamine than administration of the two drugs at separate times.

Pyridoxine hydrochloride (vitamin B6), in oral doses of 10 mg to 25 mg, may reverse the effects of levodopa by increasing the rate of aromatic amino acid decarboxylation. Carbidopa inhibits this action of pyridoxine; therefore, SINEMET can be given to patients receiving supplemental pyridoxine (vitamin B6).

Special Populations

Geriatric: A study in eight young healthy subjects (21-22 yr) and eight elderly healthy subjects (69-76 yr) showed that the absolute bioavailability of levodopa was similar between young and elderly subjects following oral administration of levodopa and carbidopa. However, the systemic exposure (AUC) of levodopa was increased by 55% in elderly subjects compared to young subjects. Based on another study in forty patients with Parkinson's disease, there was a correlation between age of patients and the increase of AUC of levodopa following administration of levodopa and an inhibitor of peripheral dopa decarboxylase. AUC of levodopa was increased by 28% in elderly patients (≥ 65 yr) compared to young patients (< 65 yr). Additionally, mean value of Cmax for levodopa was increased by 24% in elderly patients (≥ 65 yr) compared to young patients (< 65 yr) (see PRECAUTIONS, Geriatric Use).

The AUC of carbidopa was increased in elderly subjects (n=10, 65-76 yr) by 29% compared to young subjects (n=24, 23-64 yr) following IV administration of 50 mg levodopa with carbidopa (50 mg). This increase is not considered a clinically significant impact.

INDICATIONS AND USAGE

SINEMET is indicated in the treatment of Parkinson's disease, post-encephalitic parkinsonism, and symptomatic parkinsonism that may follow carbon monoxide intoxication or manganese intoxication.

Carbidopa allows patients treated for Parkinson's disease to use much lower doses of levodopa. Some patients who responded poorly to levodopa have improved on SINEMET. This is most likely due to decreased peripheral decarboxylation of levodopa caused by administration of carbidopa rather than by a primary effect of carbidopa on the nervous system. Carbidopa has not been shown to enhance the intrinsic efficacy of levodopa.

Carbidopa may also reduce nausea and vomiting and permit more rapid titration of levodopa.

CONTRAINDICATIONS

Nonselective monoamine oxidase (MAO) inhibitors are contraindicated for use with SINEMET. These inhibitors must be discontinued at least two weeks prior to initiating therapy with SINEMET. SINEMET may be administered concomitantly with the manufacturer's recommended dose of an MAO inhibitor with selectivity for MAO type B (e.g., selegiline HCl) (see PRECAUTIONS, Drug Interactions).

SINEMET is contraindicated in patients with known hypersensitivity to any component of this drug, and in patients with narrow-angle glaucoma.

WARNINGS

When SINEMET is to be given to patients who are being treated with levodopa, levodopa must be discontinued at least twelve hours before therapy with SINEMET is started. In order to reduce adverse reactions, it is necessary to individualize therapy. See DOSAGE AND ADMINISTRATION section before initiating therapy.

The addition of carbidopa with levodopa in the form of SINEMET reduces the peripheral effects (nausea, vomiting) due to decarboxylation of levodopa; however, carbidopa does not decrease the adverse reactions due to the central effects of levodopa. Because carbidopa permits more levodopa to reach the brain and more dopamine to be formed, certain adverse central nervous system (CNS) effects, e.g., dyskinesias (involuntary movements), may occur at lower dosages and sooner with SINEMET than with levodopa alone.

All patients should be observed carefully for the development of depression with concomitant suicidal tendencies.

SINEMET should be administered cautiously to patients with severe cardiovascular or pulmonary disease, bronchial asthma, renal, hepatic or endocrine disease.

As with levodopa, care should be exercised in administering SINEMET to patients with a history of myocardial infarction who have residual atrial, nodal, or ventricular arrhythmias. In such patients, cardiac function should be monitored with particular care during the period of initial dosage adjustment, in a facility with provisions for intensive cardiac care.

As with levodopa, treatment with SINEMET may increase the possibility of upper gastrointestinal hemorrhage in patients with a history of peptic ulcer.

Falling Asleep During Activities of Daily Living and Somnolence

Patients taking SINEMET alone or with other dopaminergic drugs have reported suddenly falling asleep without prior warning of sleepiness while engaged in activities of daily living (includes operation of motor vehicles). Road traffic accidents attributed to sudden sleep onset have been reported. Although many patients reported somnolence while on dopaminergic medications, there have been reports of road traffic accidents attributed to sudden onset of sleep in which the patient did not perceive any warning signs, such as excessive drowsiness, and believed that they were alert immediately prior to the event. Sudden onset of sleep has been reported to occur as long as one year after the initiation of treatment.

Falling asleep while engaged in activities of daily living usually occurs in patients experiencing pre-existing somnolence, although some patients may not give such a history. For this reason, prescribers should reassess patients for drowsiness or sleepiness especially since some of the events occur well after the start of treatment. Prescribers should be aware that patients may not acknowledge drowsiness or sleepiness until directly questioned about drowsiness or sleepiness during specific activities. Patients should be advised to exercise caution while driving or operating machines during treatment with SINEMET. Patients who have already experienced somnolence or an episode of sudden sleep onset should not participate in these activities during treatment with SINEMET.

Before initiating treatment with SINEMET, advise patients about the potential to develop drowsiness and ask specifically about factors that may increase the risk for somnolence with SINEMET such as the use of concomitant sedating medications and the presence of sleep disorders. Consider discontinuing SINEMET in patients who report significant daytime sleepiness or episodes of falling asleep during activities that require active participation (e.g., conversations, eating, etc.). If treatment with SINEMET continues, patients should be advised not to drive and to avoid other potentially dangerous activities that might result in harm if the patients become somnolent. There is insufficient information to establish that dose reduction will eliminate episodes of falling asleep while engaged in activities of daily living.

Hyperpyrexia and Confusion

Sporadic cases of a symptom complex resembling neuroleptic malignant syndrome (NMS) have been reported in association with dose reductions or withdrawal of certain antiparkinsonian agents such as levodopa, carbidopa and levodopa, or carbidopa and levodopa extended release. Therefore, patients should be observed carefully when the dosage of levodopa is reduced abruptly or discontinued, especially if the patient is receiving neuroleptics.

NMS is an uncommon but life-threatening syndrome characterized by fever or hyperthermia. Neurological findings, including muscle rigidity, involuntary movements, altered consciousness, mental status changes; other disturbances, such as autonomic dysfunction, tachycardia, tachypnea, sweating, hyper- or hypotension; laboratory findings, such as creatine phosphokinase elevation, leukocytosis, myoglobinuria, and increased serum myoglobin have been reported.

The early diagnosis of this condition is important for the appropriate management of these patients. Considering NMS as a possible diagnosis and ruling out other acute illnesses (e.g., pneumonia, systemic infection, etc.) is essential. This may be especially complex if the clinical presentation includes both serious medical illness and untreated or inadequately treated extrapyramidal signs and symptoms (EPS). Other important considerations in the differential diagnosis include central anticholinergic toxicity, heat stroke, drug fever, and primary central nervous system (CNS) pathology.

The management of NMS should include: 1) intensive symptomatic treatment and medical monitoring and 2) treatment of any concomitant serious medical problems for which specific treatments are available. Dopamine agonists, such as bromocriptine, and muscle relaxants, such as dantrolene, are often used in the treatment of NMS; however, their effectiveness has not been demonstrated in controlled studies.

PRECAUTIONS

General

As with levodopa, periodic evaluations of hepatic, hematopoietic, cardiovascular, and renal function are recommended during extended therapy.

Patients with chronic wide-angle glaucoma may be treated cautiously with SINEMET provided the intraocular pressure is well-controlled and the patient is monitored carefully for changes in intraocular pressure during therapy.

Dyskinesia

Levodopa alone, as well as SINEMET, is associated with dyskinesias. The occurrence of dyskinesias may require dosage reduction.

Hallucinations / Psychotic-Like Behavior

Hallucinations and psychotic-like behavior have been reported with dopaminergic medications. In general, hallucinations present shortly after the initiation of therapy and may be responsive to dose reduction in levodopa. Hallucinations may be accompanied by confusion and to a lesser extent sleep disorder (insomnia) and excessive dreaming.

SINEMET may have similar effects on thinking and behavior. This abnormal thinking and behavior may present with one or more symptoms, including paranoid ideation, delusions, hallucinations, confusion, psychotic-like behavior, disorientation, aggressive behavior, agitation, and delirium.

Ordinarily, patients with a major psychotic disorder should not be treated with SINEMET, because of the risk of exacerbating psychosis. In addition, certain medications used to treat psychosis may exacerbate the symptoms of Parkinson's disease and may decrease the effectiveness of SINEMET.

Impulse Control / Compulsive Behaviors

Reports of patients taking dopaminergic medications (medications that increase central dopaminergic tone), suggest that patients may experience an intense urge to gamble, increased sexual urges, intense urges to spend money, binge eating, and/or other intense urges, and the inability to control these urges. In some cases, although not all, these urges were reported to have stopped when the dose was reduced or the medication was discontinued. Because patients may not recognize these behaviors as abnormal, it is important for prescribers to specifically ask patients or the caregivers about the development of new or increased gambling urges, sexual urges, uncontrolled spending or other urges while being treated with SINEMET. Physicians should consider dose reduction or stopping the medication if a patient develops such urges while taking SINEMET [see Information for Patients].

Melanoma

Epidemiological studies have shown that patients with Parkinson's disease have a higher risk (2- to approximately 6-fold higher) of developing melanoma than the general population. Whether the increased risk observed was due to Parkinson's disease or other factors, such as drugs used to treat Parkinson's disease, is unclear.

For the reasons stated above, patients and providers are advised to monitor for melanomas frequently and on a regular basis when using SINEMET for any indication. Ideally, periodic skin examinations should be performed by appropriately qualified individuals (e.g., dermatologists).

Information for Patients

The patient should be informed that SINEMET is an immediate-release formulation of carbidopa and levodopa that is designed to begin release of ingredients within 30 minutes. It is important that SINEMET be taken at regular intervals according to the schedule outlined by the physician. The patient should be cautioned not to change the prescribed dosage regimen and not to add any additional antiparkinson medications, including other carbidopa and levodopa preparations, without first consulting the physician.

Patients should be advised that sometimes a 'wearing-off' effect may occur at the end of the dosing interval. The physician should be notified if such response poses a problem to lifestyle.

Patients should be advised that occasionally, dark color (red, brown, or black) may appear in saliva, urine, or sweat after ingestion of SINEMET. Although the color appears to be clinically insignificant, garments may become discolored.

The patient should be advised that a change in diet to foods that are high in protein may delay the absorption of levodopa and may reduce the amount taken up in the circulation. Excessive acidity also delays stomach emptying, thus delaying the absorption of levodopa. Iron salts (such as in multivitamin tablets) may also reduce the amount of levodopa available to the body. The above factors may reduce the clinical effectiveness of the levodopa or carbidopa and levodopa therapy.

Patients should be alerted to the possibility of sudden onset of sleep during daily activities, in some cases without awareness or warning signs, when they are taking dopaminergic agents, including levodopa. Patients should be advised to exercise caution while driving or operating machinery and that if they have experienced somnolence and/or sudden sleep onset, they must refrain from these activities. (See WARNINGS, Falling Asleep During Activities of Daily Living and Somnolence.)

There have been reports of patients experiencing intense urges to gamble, increased sexual urges, and other intense urges, and the inability to control these urges while taking one or more of the medications that increase central dopaminergic tone and that are generally used for the treatment of Parkinson's disease, including SINEMET. Although it is not proven that the medications caused these events, these urges were reported to have stopped in some cases when the dose was reduced or the medication was stopped. Prescribers should ask patients about the development of new or increased gambling urges, sexual urges or other urges while being treated with SINEMET. Patients should inform their physician if they experience new or increased gambling urges, increased sexual urges, or other intense urges while taking SINEMET. Physicians should consider dose reduction or stopping the medication if a patient develops such urges while taking SINEMET (See PRECAUTIONS, Impulse Control / Compulsive Behaviors).

Laboratory Tests

Abnormalities in laboratory tests may include elevations of liver function tests such as alkaline phosphatase, SGOT (AST), SGPT (ALT), lactic dehydrogenase (LDH), and bilirubin. Abnormalities in blood urea nitrogen (BUN) and positive Coombs test have also been reported. Commonly, levels of blood urea nitrogen, creatinine, and uric acid are lower during administration of SINEMET than with levodopa.

SINEMET may cause a false-positive reaction for urinary ketone bodies when a test tape is used for determination of ketonuria. This reaction will not be altered by boiling the urine specimen. False-negative tests may result with the use of glucose-oxidase methods of testing for glucosuria.

Cases of falsely diagnosed pheochromocytoma in patients on carbidopa and levodopa therapy have been reported very rarely. Caution should be exercised when interpreting the plasma and urine levels of catecholamines and their metabolites in patients on levodopa or carbidopa and levodopa therapy.

Drug Interactions

Caution should be exercised when the following drugs are administered concomitantly with SINEMET.

Symptomatic postural hypotension occurred when SINEMET was added to the treatment of a patient receiving antihypertensive drugs. Therefore, when therapy with SINEMET is started, dosage adjustment of the antihypertensive drug may be required.

For patients receiving MAO inhibitors (Type A or B), see CONTRAINDICATIONS. Concomitant therapy with selegiline and carbidopa and levodopa may be associated with severe orthostatic hypotension not attributable to carbidopa and levodopa alone (see CONTRAINDICATIONS).

There have been rare reports of adverse reactions, including hypertension and dyskinesia, resulting from the concomitant use of tricyclic antidepressants and SINEMET.

Dopamine D2 receptor antagonists (e.g., phenothiazines, butyrophenones, risperidone) and isoniazid may reduce the therapeutic effects of levodopa. In addition, the beneficial effects of levodopa in Parkinson's disease have been reported to be reversed by phenytoin and papaverine. Patients taking these drugs with SINEMET should be carefully observed for loss of therapeutic response.

Use of SINEMET with dopamine-depleting agents (e.g., reserpine and tetrabenazine) or other drugs known to deplete monoamine stores is not recommended.

SINEMET and iron salts or multivitamins containing iron salts should be coadministered with caution. Iron salts can form chelates with levodopa and carbidopa and consequently reduce the bioavailability of carbidopa and levodopa.

Although metoclopramide may increase the bioavailability of levodopa by increasing gastric emptying, metoclopramide may also adversely affect disease control by its dopamine receptor antagonistic properties.

Carcinogenesis, Mutagenesis, Impairment of Fertility

In a two-year bioassay of SINEMET, no evidence of carcinogenicity was found in rats receiving doses of approximately two times the maximum daily human dose of carbidopa and four times the maximum daily human dose of levodopa.

In reproduction studies with SINEMET, no effects on fertility were found in rats receiving doses of approximately two times the maximum daily human dose of carbidopa and four times the maximum daily human dose of levodopa.

Pregnancy

No teratogenic effects were observed in a study in mice receiving up to 20 times the maximum recommended human dose of SINEMET. There was a decrease in the number of live pups delivered by rats receiving approximately two times the maximum recommended human dose of carbidopa and approximately five times the maximum recommended human dose of levodopa during organogenesis. SINEMET caused both visceral and skeletal malformations in rabbits at all doses and ratios of carbidopa/levodopa tested, which ranged from 10 times/5 times the maximum recommended human dose of carbidopa/levodopa to 20 times/10 times the maximum recommended human dose of carbidopa/levodopa.

There are no adequate or well-controlled studies in pregnant women. It has been reported from individual cases that levodopa crosses the human placental barrier, enters the fetus, and is metabolized. Carbidopa concentrations in fetal tissue appeared to be minimal. Use of SINEMET in women of childbearing potential requires that the anticipated benefits of the drug be weighed against possible hazards to mother and child.

Nursing Mothers

Levodopa has been detected in human milk. Caution should be exercised when SINEMET is administered to a nursing woman.

Pediatric Use

Safety and effectiveness in pediatric patients have not been established. Use of the drug in patients below the age of 18 is not recommended.

Geriatric Use

In the clinical efficacy trials for SINEMET, almost half of the patients were older than 65, but few were older than 75. No overall meaningful differences in safety or effectiveness were observed between these subjects and younger subjects, but greater sensitivity of some older individuals to adverse drug reactions such as hallucinations cannot be ruled out. There is no specific dosing recommendation based upon clinical pharmacology data as SINEMET is titrated as tolerated for clinical effect.

ADVERSE REACTIONS

The most common adverse reactions reported with SINEMET have included dyskinesias, such as choreiform, dystonic, and other involuntary movements, and nausea.

The following other adverse reactions have been reported with SINEMET:

Body as a Whole

Chest pain, asthenia.

Cardiovascular

Cardiac irregularities, hypotension, orthostatic effects including orthostatic hypotension, hypertension, syncope, phlebitis, palpitation.

Gastrointestinal

Dark saliva, gastrointestinal bleeding, development of duodenal ulcer, anorexia, vomiting, diarrhea, constipation, dyspepsia, dry mouth, taste alterations.

Hematologic

Agranulocytosis, hemolytic and non-hemolytic anemia, thrombocytopenia, leukopenia.

Hypersensitivity

Angioedema, urticaria, pruritus, Henoch-Schönlein purpura, bullous lesions (including pemphigus-like reactions).

Musculoskeletal

Back pain, shoulder pain, muscle cramps.

Nervous System/Psychiatric

Psychotic episodes including delusions, hallucinations, and paranoid ideation, bradykinetic episodes ("on-off" phenomenon), confusion, agitation, dizziness, somnolence, dream abnormalities including nightmares, insomnia, paresthesia, headache, depression with or without development of suicidal tendencies, dementia, pathological gambling, increased libido including hypersexuality, impulse control symptoms. Convulsions also have occurred; however, a causal relationship with SINEMET has not been established.

Respiratory

Dyspnea, upper respiratory infection.

Skin

Rash, increased sweating, alopecia, dark sweat.

Urogenital

Urinary tract infection, urinary frequency, dark urine.

Laboratory Tests

Decreased hemoglobin and hematocrit; abnormalities in alkaline phosphatase, SGOT (AST), SGPT (ALT), LDH, bilirubin, BUN, Coombs test; elevated serum glucose; white blood cells, bacteria, and blood in the urine.

Other adverse reactions that have been reported with levodopa alone and with various carbidopa and levodopa formulations, and may occur with SINEMET are:

Body as a Whole

Abdominal pain and distress, fatigue.

Cardiovascular

Myocardial infarction.

Gastrointestinal

Gastrointestinal pain, dysphagia, sialorrhea, flatulence, bruxism, burning sensation of the tongue, heartburn, hiccups.

Metabolic

Edema, weight gain, weight loss.

Musculoskeletal

Leg pain.

Nervous System/Psychiatric

Ataxia, extrapyramidal disorder, falling, anxiety, gait abnormalities, nervousness, decreased mental acuity, memory impairment, disorientation, euphoria, blepharospasm (which may be taken as an early sign of excess dosage; consideration of dosage reduction may be made at this time), trismus, increased tremor, numbness, muscle twitching, activation of latent Horner's syndrome, peripheral neuropathy.

Respiratory

Pharyngeal pain, cough.

Skin

Malignant melanoma, flushing.

Special Senses

Oculogyric crises, diplopia, blurred vision, dilated pupils.

Urogenital

Urinary retention, urinary incontinence, priapism.

Miscellaneous

Bizarre breathing patterns, faintness, hoarseness, malaise, hot flashes, sense of stimulation.

Laboratory Tests

Decreased white blood cell count and serum potassium; increased serum creatinine and uric acid; protein and glucose in urine.

OVERDOSAGE

Management of acute overdosage with SINEMET is the same as management of acute overdosage with levodopa. Pyridoxine is not effective in reversing the actions of SINEMET.

General supportive measures should be employed, along with immediate gastric lavage. Intravenous fluids should be administered judiciously and an adequate airway maintained. Electrocardiographic monitoring should be instituted and the patient carefully observed for the development of arrhythmias; if required, appropriate antiarrhythmic therapy should be given. The possibility that the patient may have taken other drugs as well as SINEMET should be taken into consideration. To date, no experience has been reported with dialysis; hence, its value in overdosage is not known.

Based on studies in which high doses of levodopa and/or carbidopa were administered, a significant proportion of rats and mice given single oral doses of levodopa of approximately 1500-2000 mg/kg are expected to die. A significant proportion of infant rats of both sexes are expected to die at a dose of 800 mg/kg. A significant proportion of rats are expected to die after treatment with similar doses of carbidopa. The addition of carbidopa in a 1:10 ratio with levodopa increases the dose at which a significant proportion of mice are expected to die to 3360 mg/kg.

DOSAGE AND ADMINISTRATION

The optimum daily dosage of SINEMET must be determined by careful titration in each patient. SINEMET tablets are available in a 1:4 ratio of carbidopa to levodopa (SINEMET 25-100) as well as 1:10 ratio (SINEMET 25-250 and SINEMET 10-100). Tablets of the two ratios may be given separately or combined as needed to provide the optimum dosage.

Studies show that peripheral dopa decarboxylase is saturated by carbidopa at approximately 70 to 100 mg a day. Patients receiving less than this amount of carbidopa are more likely to experience nausea and vomiting.

Usual Initial Dosage

Dosage is best initiated with one tablet of SINEMET 25-100 three times a day. This dosage schedule provides 75 mg of carbidopa per day. Dosage may be increased by one tablet every day or every other day, as necessary, until a dosage of eight tablets of SINEMET 25-100 a day is reached.

If SINEMET 10-100 is used, dosage may be initiated with one tablet three or four times a day. However, this will not provide an adequate amount of carbidopa for many patients. Dosage may be increased by one tablet every day or every other day until a total of eight tablets (2 tablets q.i.d.) is reached.

How to Transfer Patients from Levodopa

Levodopa must be discontinued at least twelve hours before starting SINEMET. A daily dosage of SINEMET should be chosen that will provide approximately 25% of the previous levodopa dosage. Patients who are taking less than 1500 mg of levodopa a day should be started on one tablet of SINEMET 25-100 three or four times a day. The suggested starting dosage for most patients taking more than 1500 mg of levodopa is one tablet of SINEMET 25-250 three or four times a day.

Maintenance

Therapy should be individualized and adjusted according to the desired therapeutic response. At least 70 to 100 mg of carbidopa per day should be provided. When a greater proportion of carbidopa is required, one tablet of SINEMET 25-100 may be substituted for each tablet of SINEMET 10-100. When more levodopa is required, SINEMET 25-250 should be substituted for SINEMET 25-100 or SINEMET 10-100. If necessary, the dosage of carbidopa and levodopa 25-250 may be increased by one-half or one tablet every day or every other day to a maximum of eight tablets a day. Experience with total daily dosages of carbidopa greater than 200 mg is limited.

Because both therapeutic and adverse responses occur more rapidly with SINEMET than with levodopa alone, patients should be monitored closely during the dose adjustment period. Specifically, involuntary movements will occur more rapidly with SINEMET than with levodopa. The occurrence of involuntary movements may require dosage reduction. Blepharospasm may be a useful early sign of excess dosage in some patients.

Addition of Other Antiparkinsonian Medications

Standard drugs for Parkinson's disease, other than levodopa without a decarboxylase inhibitor, may be used concomitantly while SINEMET is being administered, although dosage adjustments may be required.

Interruption of Therapy

Sporadic cases of hyperpyrexia and confusion have been associated with dose reductions and withdrawal of SINEMET. Patients should be observed carefully if abrupt reduction or discontinuation of SINEMET is required, especially if the patient is receiving neuroleptics. (See WARNINGS.)

If general anesthesia is required, SINEMET may be continued as long as the patient is permitted to take fluids and medication by mouth. If therapy is interrupted temporarily, the patient should be observed for symptoms resembling NMS, and the usual daily dosage may be administered as soon as the patient is able to take oral medication.

HOW SUPPLIED

SINEMET 25-100 Tablets are yellow oval tablets that are plain on one side, with "650" and a score line on the other. They are supplied as follows:

NDC 78206-168-01 bottles of 100.

SINEMET 25-100 Tablets are yellow oval tablets that are plain on one side, with “650” on the other. They are supplied as follows:

NDC 78206-190-01 bottles of 100.

SINEMET 10-100 Tablets are dark dapple-blue oval tablets that are plain on one side, with "647" and a score line on the other. They are supplied as follows:

NDC 78206-166-01 bottles of 100.

SINEMET 25-250 Tablets are light dapple-blue oval tablets that are plain on one side, with "654" and a score line on the other. They are supplied as follows:

NDC 78206-167-01 bottles of 100.

Storage and Handling

Store at 25°C (77°F), excursions permitted to 15-30°C (59-86°F) [see USP Controlled Room Temperature]. Store in a tightly closed container, protected from light and moisture.

Dispense in a tightly closed, light-resistant container.

Distributed by: Organon LLC, a subsidiary of
ORGANON & Co.,
Jersey City, NJ 07302, USA

For patent information: www.organon.com/our-solutions/patent/

© 2024 Organon group of companies. All rights reserved.

Revised: 10/2024

uspi-og0295b-t-2410r001

Rx Only

PRINCIPAL DISPLAY PANEL - 10 mg/100 mg Tablet Bottle Label

NDC 78206-166-01

Sinemet®
(carbidopa and levodopa)
Tablets

10 mg/100 mg

Each tablet contains 10 mg carbidopa
(anhydrous equivalent) and 100 mg levodopa.

Store at 25°C (77°F), excursions permitted to
15-30°C (59-86°F) [see USP Controlled Room
Temperature]. Store in a tightly closed container,
protected from light and moisture.

Rx only

100 Tablets

PRINCIPAL DISPLAY PANEL - 25 mg/100 mg Tablet Bottle Label

NDC 78206-168-01

Sinemet®
(carbidopa and levodopa)
Tablets

25 mg/100 mg

Each tablet contains 25 mg carbidopa
(anhydrous equivalent) and 100 mg levodopa.

Store at 25°C (77°F), excursions permitted to
15-30°C (59-86°F) [see USP Controlled Room
Temperature]. Store in a tightly closed container,
protected from light and moisture.

Rx only

100 Tablets

PRINCIPAL DISPLAY PANEL - 25 mg/250 mg Tablet Bottle Label

NDC 78206-167-01

Sinemet®
(carbidopa and levodopa)
Tablets

25 mg/250 mg

Each tablet contains 25 mg carbidopa
(anhydrous equivalent) and 250 mg levodopa.

Store at 25°C (77°F), excursions permitted to
15-30°C (59-86°F) [see USP Controlled Room
Temperature]. Store in a tightly closed container,
protected from light and moisture.

Rx only

100 Tablets

PRINCIPAL DISPLAY PANEL - 25 mg/100 mg Tablet Bottle Label

NDC 78206-190-01

Sinemet®
(carbidopa and levodopa)
Tablets

25 mg /100 mg

Each tablet contains 25 mg carbidopa
(anhydrous equivalent) and 100 mg levodopa.

Store at 25°C (77°F), excursions permitted to
15-30°C (59-86°F) [see USP Controlled Room
Temperature]. Store in a tightly closed container,
protected from light and moisture.

Rx only

100 Tablets